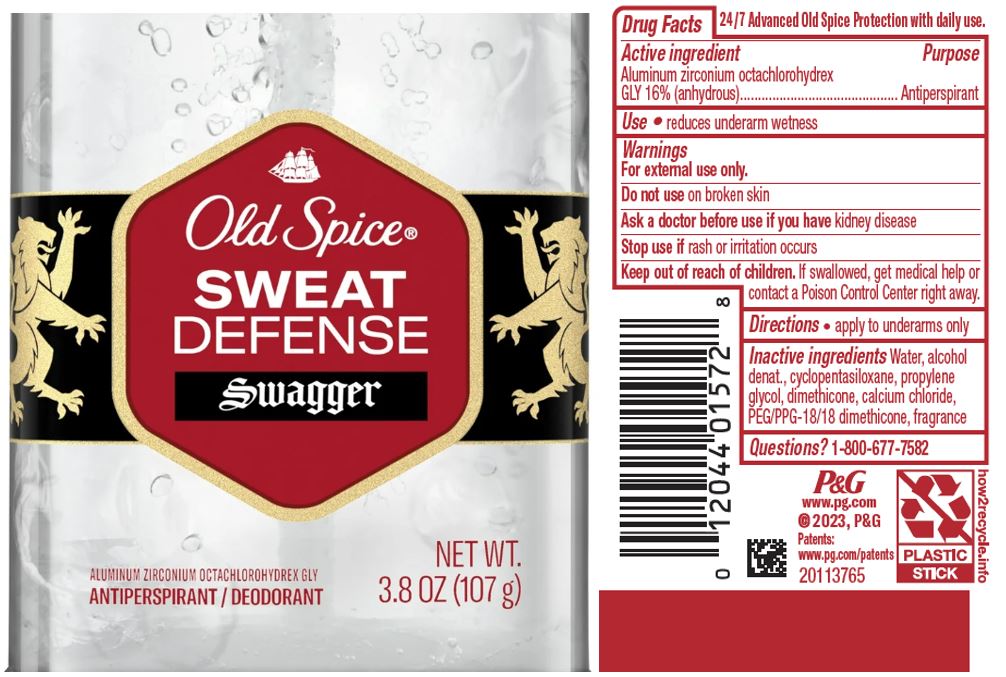 DRUG LABEL: Old Spice Sweat Defense Swagger Clear
NDC: 84126-009 | Form: GEL
Manufacturer: The Procter & Gamble Manufacturing Company
Category: otc | Type: HUMAN OTC DRUG LABEL
Date: 20251231

ACTIVE INGREDIENTS: ALUMINUM ZIRCONIUM OCTACHLOROHYDREX GLY 16 g/100 g
INACTIVE INGREDIENTS: CYCLOMETHICONE 5; DIMETHICONE; PROPYLENE GLYCOL; ALCOHOL; CALCIUM CHLORIDE; PEG/PPG-18/18 DIMETHICONE; WATER

Old Spice® Sweat Defense Swagger Clear Gel

Drug Facts

Active ingredient

Aluminum zirconium octachlorohydrex Gly 16% (anhydrous)

Purpose

Antiperspirant

Use

- reduces underarm wetness

Warnings

For external use only.

Do not use on broken skin

Ask a doctor before use if you have kidney disease

Stop use if rash or irritation occurs

Keep out of reach of children. If swallowed, get medical help or contact a Poison Control Center right away.

Directions

apply to underarms only

Inactive ingredients

Water, alcohol denat., cyclopentasiloxane, propylene glycol, dimethicone, calcium chloride, PEG/PPG-18/18 dimethicone, fragrance

Questions?

1-800-677-7582

Dist. by PROCTER & GAMBLE,
CINCINNATI, OH 45202.

PRINCIPAL DISPLAY - 107 g canister label

Old Spice ®

SWEAT
DEFENSE

SWAGGER

Clear Gel

ALUMINUM ZIRCONIUM OCTACHLOROHYDREX GLY
ANTI-PERSPIRANT/DEODORANT

NET WT. 3.8 OZ (107 g)